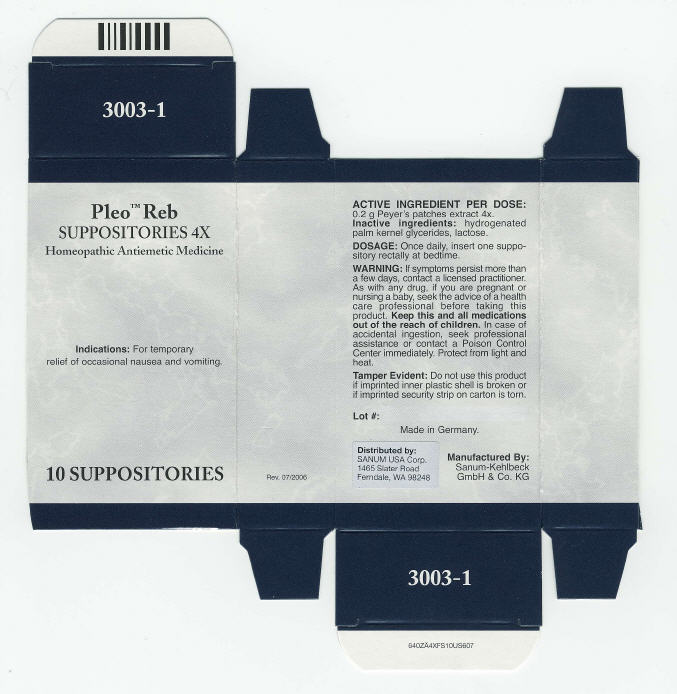 DRUG LABEL: Pleo Reb
NDC: 60681-3003 | Form: SUPPOSITORY
Manufacturer: Sanum Kehlbeck GmbH & Co. KG
Category: homeopathic | Type: HUMAN OTC DRUG LABEL
Date: 20100106

ACTIVE INGREDIENTS: sus scrofa small intestine mucosa lymph follicle 4 [hp_X]/1 1
INACTIVE INGREDIENTS: lactose

Pleo™ Reb
SUPPOSITORIES 4X

Homeopathic Antiemetic Medicine

10 SUPPOSITORIES

Indications

For temporary relief of occasional nausea and vomiting.

ACTIVE INGREDIENT PER DOSE

0.2 g Peyer's patches extract 4x.

Inactive ingredients

hydrogenated palm kernel glycerides, lactose.

DOSAGE

Once daily, insert one suppository rectally at bedtime.

WARNING

If symptoms persist more than a few days, contact a licensed practitioner. As with any drug, if you are pregnant or nursing a baby, seek the advice of a health care professional before taking this product.

KEEP OUT OF REACH OF CHILDREN

Keep this and all medications out of the reach of children. In case of accidental ingestion, seek professional assistance or contact a Poison Control Center immediately.

STORAGE AND HANDLING

Protect from light and heat.

Tamper Evident

Do not use this product if imprinted inner plastic shell is broken or if imprinted security strip on carton is torn.

Made in Germany.

Distributed by:
SANUM USA Corp.
1465 Slater Road
Ferndale, WA 98248

Manufactured By:
Sanum-Kehlbeck
GmbH & Co. KG

Rev. 07/2006

PRINCIPAL DISPLAY PANEL - 10 Suppositories Carton

Pleo™ Reb
SUPPOSITORIES 4X

Homeopathic Antiemetic Medicine

Indications: For temporary
relief of occasional nausea and vomiting.

10 SUPPOSITORIES